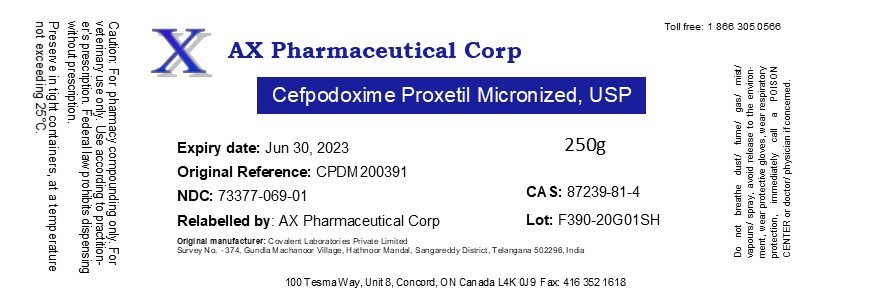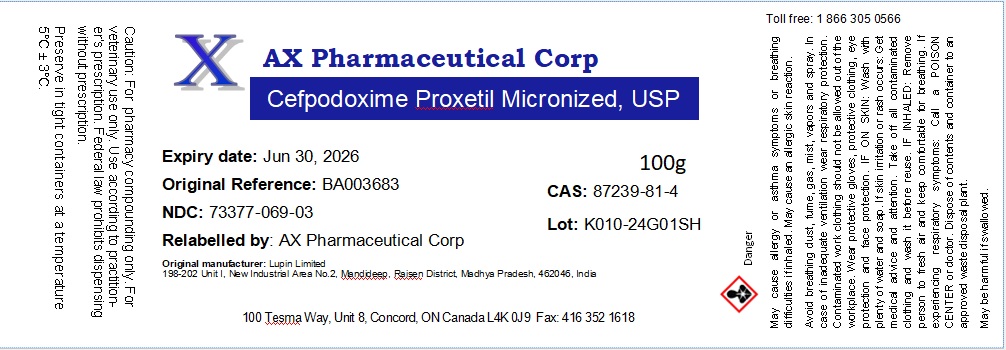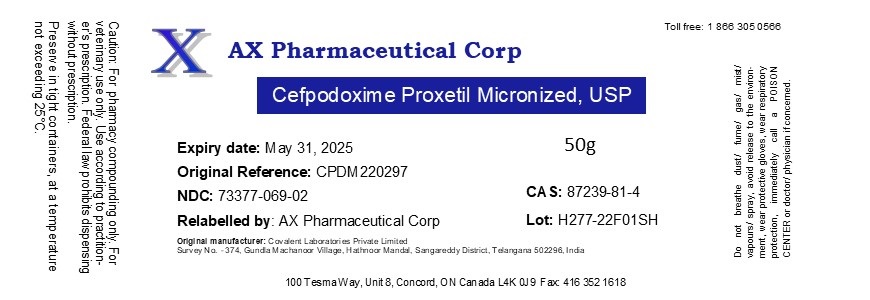 DRUG LABEL: Cefpodoxime Proxetil
NDC: 73377-069 | Form: POWDER
Manufacturer: AX Pharmaceutical Corp
Category: other | Type: BULK INGREDIENT - ANIMAL DRUG
Date: 20260116

ACTIVE INGREDIENTS: CEFPODOXIME PROXETIL 1 g/1 g

Cefpodoxime Proxetil